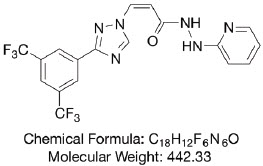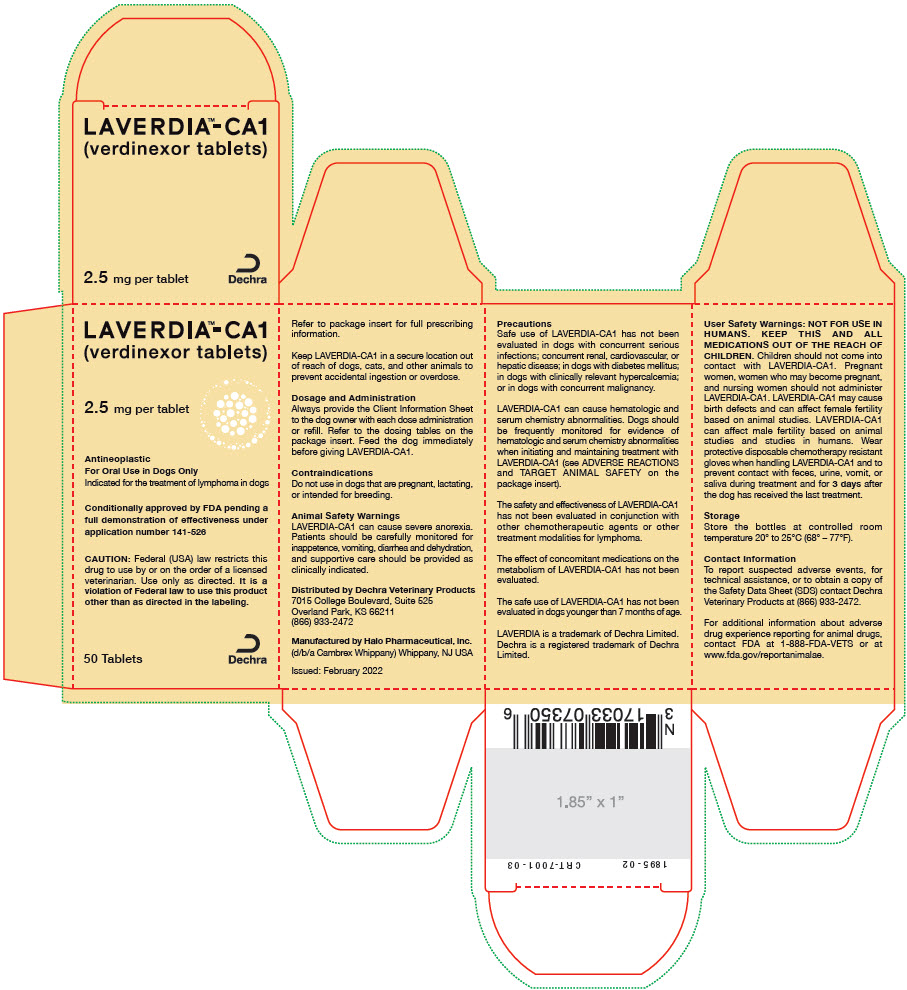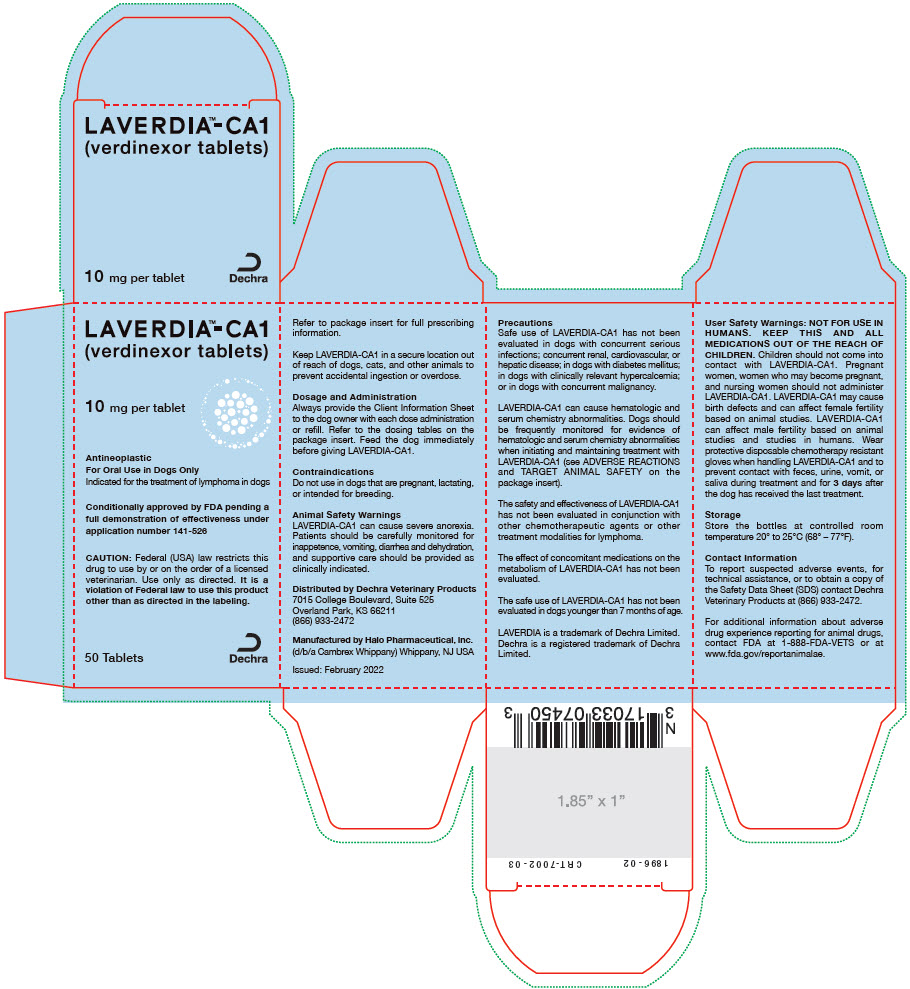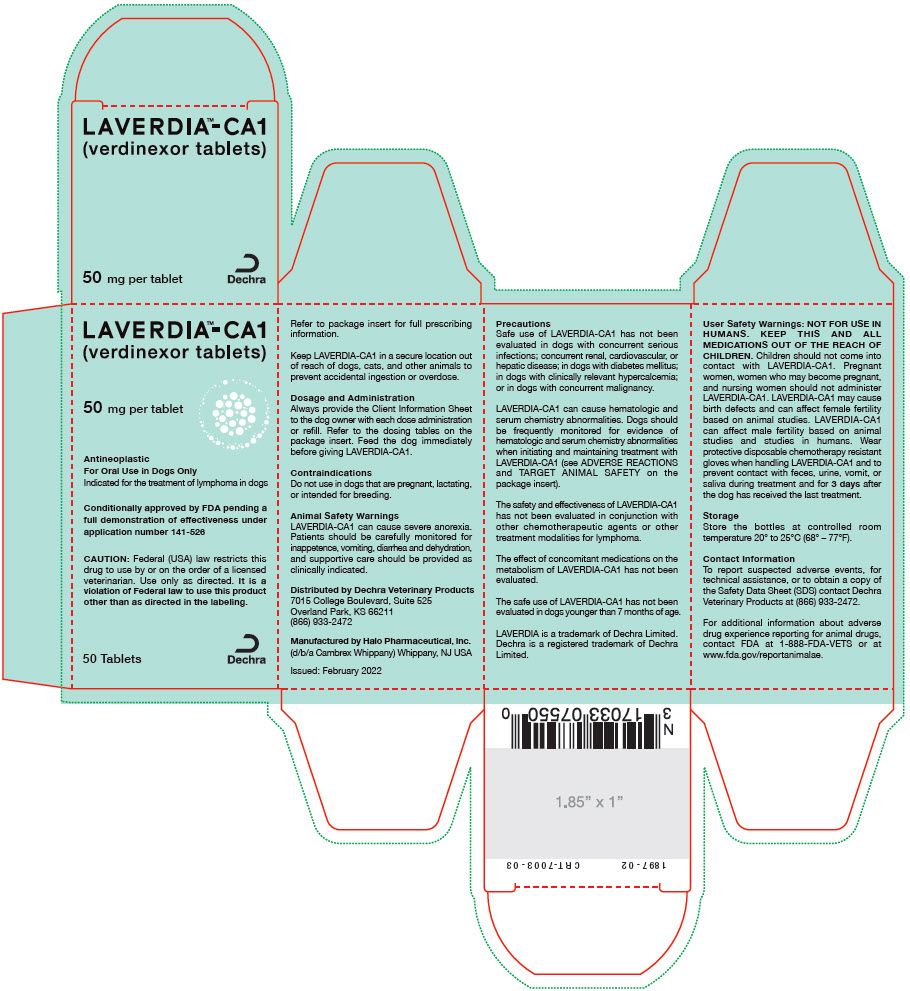 DRUG LABEL: Laverdia-CA1
NDC: 17033-073 | Form: TABLET, COATED
Manufacturer: Dechra Veterinary Products
Category: animal | Type: PRESCRIPTION ANIMAL DRUG LABEL
Date: 20230228

ACTIVE INGREDIENTS: verdinexor 2.5 mg/1 1
INACTIVE INGREDIENTS: Microcrystalline Cellulose; Croscarmellose Sodium; POVIDONE, UNSPECIFIED; SILICON DIOXIDE; Magnesium Stearate; Sodium Lauryl Sulfate

LAVERDIA™-CA1
(verdinexor tablets)

Conditionally approved by FDA pending a full demonstration of effectiveness under application number 141-526

2.5 mg ∙ 10 mg ∙ 50 mg

Coated Tablets
Antineoplastic

For oral use in dogs only

CAUTION: Federal (USA) law restricts this drug to use by or on the order of a licensed veterinarian. Use only as directed. It is a violation of Federal law to use this product other than as directed in the labeling.

DESCRIPTION

DESCRIPTION: LAVERDIA-CA1 (verdinexor tablets) is a selective inhibitor of nuclear export (SINE) that blocks chromosome region maintenance 1 (CRM1).

LAVERDIA-CA1 has the following structural formula:

INDICATIONS AND USAGE

INDICATION: LAVERDIA-CA1 is indicated for the treatment of lymphoma in dogs.

DOSAGE AND ADMINISTRATION: Always provide the Client Information Sheet to the dog owner with each prescription.

Dosing Instructions:

1. Feed the dog immediately before giving LAVERDIA-CA1.

2. Wear protective disposable chemotherapy resistant gloves when handling LAVERDIA-CA1 (see USER SAFETY WARNINGS).

3. Administer LAVERDIA-CA1 at an initial dose of 1.25 mg/kg administered orally twice per week (e.g., Monday and Thursday or Tuesday and Friday) with at least 72 hours between doses (see Table 1).

4. If tolerated after 2 weeks, increase the dose of LAVERDIA-CA1 to 1.5 mg/kg twice per week with at least 72 hours between doses (see Table 2).

5. Dose reductions of 0.25 mg/kg to a minimum dose of 1 mg/kg twice per week with at least 72 hours between doses (see Table 3) or dose interruptions may be considered as a result of adverse reactions (See ANIMAL SAFETY WARNINGS, PRECAUTIONS, and ADVERSE REACTIONS).

6. Do not split or crush tablets.

Dosing Restrictions:

Dogs weighing less than 9 kg may not be accurately dosed or undergo dose adjustments.

LAVERDIA-CA1 cannot be accurately increased in dose from 1.25 mg/kg to 1.5 mg/kg in dogs weighing 9 to 9.6 kg because the dose administered remains the same.

Dosing Tables:

Table 1. LAVERDIA-CA1 dose table for the 1.25 mg/kg dose [Use an appropriate combination of tablets to dose dogs over 61.5 kg.]
 |  | Number of Tablets
Dog weight (kg) | Total mg to administer | 2.5 mg tablets | 10 mg tablets | 50 mg tablets
9 — 11.5 | 12.5 | 1 | 1 | -
11.6 — 13.5 | 15 | 2 | 1 | -
13.6 — 15.5 | 17.5 | 3 | 1 | -
15.6 — 17.5 | 20 | - | 2 | -
17.6 — 19.5 | 22.5 | 1 | 2 | -
19.6 — 21.5 | 25 | 2 | 2 | -
21.6 — 23.5 | 27.5 | 3 | 2 | -
23.6 — 25.5 | 30 | - | 3 | -
25.6 — 27.5 | 32.5 | 1 | 3 | -
27.6 — 29.5 | 35 | 2 | 3 | -
29.6 — 31.5 | 37.5 | 3 | 3 | -
31.6 — 33.5 | 40 | - | 4 | -
33.6 — 35.5 | 42.5 | 1 | 4 | -
35.6 — 37.5 | 45 | 2 | 4 | -
37.6 — 39.5 | 47.5 | 3 | 4 | -
39.6 — 41.5 | 50 | - | - | 1
41.6 — 43.5 | 52.5 | 1 | - | 1
43.6 — 45.5 | 55 | 2 | - | 1
45.6 — 47.5 | 57.5 | 3 | - | 1
47.6 — 49.5 | 60 | - | 1 | 1
49.6 — 51.5 | 62.5 | 1 | 1 | 1
51.6 — 53.5 | 65 | 2 | 1 | 1
53.6 — 55.5 | 67.5 | 3 | 1 | 1
55.6 — 57.5 | 70 | - | 2 | 1
57.6 — 59.5 | 72.5 | 1 | 2 | 1
59.6 — 61.5 | 75 | 2 | 2 | 1

Table 2. LAVERDIA-CA1 dose table for the 1.5 mg/kg dose [Use an appropriate combination of tablets to dose dogs over 61.3 kg.]
 |  | Number of Tablets
Dog weight (kg) | Total mg to administer | 2.5 mg tablets | 10 mg tablets | 50 mg tablets
9.7 — 11.3 | 15 | 2 | 1 | -
11.4 — 12.9 | 17.5 | 3 | 1 | -
13 — 14.6 | 20 | - | 2 | -
14.7 — 16.3 | 22.5 | 1 | 2 | -
16.4 — 17.9 | 25 | 2 | 2 | -
18 — 19.6 | 27.5 | 3 | 2 | -
19.7 — 21.3 | 30 | - | 3 | -
21.4 — 22.9 | 32.5 | 1 | 3 | -
23 — 24.6 | 35 | 2 | 3 | -
24.7 — 26.3 | 37.5 | 3 | 3 | -
26.4 — 27.9 | 40 | - | 4 | -
28 — 29.6 | 42.5 | 1 | 4 | -
29.7 — 31.3 | 45 | 2 | 4 | -
31.4 — 32.9 | 47.5 | 3 | 4 | -
33 — 34.6 | 50 | - | - | 1
34.7 — 36.3 | 52.5 | 1 | - | 1
36.4 — 37.9 | 55 | 2 | - | 1
38 — 39.6 | 57.5 | 3 | - | 1
39.7 — 41.3 | 60 | - | 1 | 1
41.4 — 42.9 | 62.5 | 1 | 1 | 1
43 — 44.6 | 65 | 2 | 1 | 1
44.7 — 46.3 | 67.5 | 3 | 1 | 1
46.4 — 47.9 | 70 | - | 2 | 1
48 — 49.6 | 72.5 | 1 | 2 | 1
49.7 — 51.3 | 75 | 2 | 2 | 1
51.4 — 52.9 | 77.5 | 3 | 2 | 1
53 — 54.6 | 80 | - | 3 | 1
54.7 — 56.3 | 82.5 | 1 | 3 | 1
56.4 — 57.9 | 85 | 2 | 3 | 1
58 — 59.6 | 87.5 | 3 | 3 | 1
59.7 — 61.3 | 90 | - | 4 | 1

Table 3. LAVERDIA-CA1 dose table for the 1 mg/kg dose [Use an appropriate combination of tablets to dose dogs over 61.9 kg.]
 |  | Number of Tablets
Dog weight (kg) | Total mg to administer | 2.5 mg tablets | 10 mg tablets | 50 mg tablets
9 — 11.9 | 10 | - | 1 | -
12 — 14.4 | 12.5 | 1 | 1 | -
14.5 — 16.9 | 15 | 2 | 1 | -
17 — 19.4 | 17.5 | 3 | 1 | -
19.5 — 21.9 | 20 | - | 2 | -
22 — 24.4 | 22.5 | 1 | 2 | -
24.5 — 26.9 | 25 | 2 | 2 | -
27 — 29.4 | 27.5 | 3 | 2 | -
29.5 — 31.9 | 30 | - | 3 | -
32 — 34.4 | 32.5 | 1 | 3 | -
34.5 — 36.9 | 35 | 2 | 3 | -
37 — 39.4 | 37.5 | 3 | 3 | -
39.5 — 41.9 | 40 | - | 4 | -
42 — 44.4 | 42.5 | 1 | 4 | -
44.5 — 46.9 | 45 | 2 | 4 | -
47 — 49.4 | 47.5 | 3 | 4 | -
49.5 — 51.9 | 50 | - | - | 1
52 — 54.4 | 52.5 | 1 | - | 1
54.5 — 56.9 | 55 | 2 | - | 1
57 — 59.4 | 57.5 | 3 | - | 1
59.5 — 61.9 | 60 | - | 1 | 1

CONTRAINDICATIONS:

Do not use in dogs that are pregnant, lactating or intended for breeding. LAVERDIA-CA1 is a possible teratogen and can affect female and male fertility. Laboratory studies in the rat have shown reduced fertility, embryotoxicity, teratogenicity, and maternal toxicity. Administration of LAVERDIA-CA1 caused degeneration/atrophy and vacuolation in the seminiferous tubules and oligospermia in the epididymides in male dogs in the margin of safety study (see TARGET ANIMAL SAFETY).

WARNINGS:

USER SAFETY WARNINGS:

NOT FOR USE IN HUMANS. KEEP THIS AND ALL MEDICATIONS OUT OF THE REACH OF CHILDREN. CHILDREN SHOULD NOT COME INTO CONTACT WITH LAVERDIA-CA1. Children should not come in contact with the feces, urine, vomit, or saliva of treated dogs.

Pregnant women, women who may become pregnant, and nursing women should not handle or administer LAVERDIA-CA1 or come in contact with the feces, urine, vomit, or saliva from LAVERDIA-CA1-treated dogs. LAVERDIA-CA1 may cause birth defects and can affect female fertility based on animal studies.

LAVERDIA-CA1 can affect male fertility based on animal studies and studies in humans.

Wear protective disposable chemotherapy resistant gloves when handling LAVERDIA-CA1 to avoid exposure to drug.

Wear protective disposable chemotherapy resistant gloves to prevent direct contact with moistened, broken, or crushed LAVERDIA-CA1 tablets.

Wear protective disposable chemotherapy resistant gloves to prevent contact with feces, urine, vomit, and saliva during treatment and for 3 days after the dog has received the last treatment. Place all waste material in a plastic bag and seal before general disposal. Wash hands immediately and thoroughly with soap and water if contact occurs with the feces, urine, vomit, or saliva from LAVERDIA-CA1 treated dogs.

Any items that come in contact with feces, urine, vomit, or saliva should not be washed with other laundry during treatment and for 3 days after the last treatment with LAVERDIA-CA1.

Wear protective disposable chemotherapy resistant gloves when handling the dog's toys, food bowl, and water bowl. Wash food and water bowls separately from other items during treatment and for 3 days after the dog has received the last treatment.

If LAVERDIA-CA1 is accidentally ingested, or if there is significant contact with feces, urine, vomit, or saliva of dogs during treatment or within 3 days after the last treatment without proper precautions, seek medical advice immediately. It is important to show the treating physician a copy of the package insert, label, or client information sheet.

Special instructions for handling and administering the product

- It is recommended that LAVERDIA-CA1 be administered under the supervision of, or in consultation with, a veterinarian experienced in the use of cancer therapeutic agents.
- Use standard measures for the safe handling of all chemotherapeutic drugs. Refer to Occupational Safety and Health Administration (OSHA) for appropriate guidelines, recommendations, and regulations for handling antineoplastic agents.
- Do not eat, drink, or smoke while handling the product.
- Do not store near food, in or near a food preparation area, or with medications intended for use in humans.

Skin contact

- In case of contact with the skin, wash the affected area immediately and thoroughly with soap and water.

Accidental eye exposure

- Rinse the eyes with large amounts of tap water (use eyewash station if present) for 10 minutes while holding back the eyelid.
- Remove contact lenses.
- Seek medical advice immediately and show the package insert or label to the physician.

Accidental oral exposure or ingestion

- Seek medical advice immediately and show the package insert or label to the physician.

ANIMAL SAFETY WARNINGS:

LAVERDIA-CA1 can cause severe anorexia. Patients should be carefully monitored for inappetence, vomiting, diarrhea and dehydration, and supportive care should be provided as clinically indicated (see ADVERSE REACTIONS). In the study used to support reasonable expectation of effectiveness, low doses of corticosteroids (prednisone) were found to reduce the incidence of anorexia and gastrointestinal adverse reactions associated with verdinexor.

Keep LAVERDIA-CA1 in a secure location out of reach of dogs, cats, and other animals to prevent accidental ingestion or overdose.

PRECAUTIONS:

Safe use of LAVERDIA-CA1 has not been evaluated in dogs with concurrent serious infections; concurrent renal, cardiovascular, or hepatic disease; in dogs with diabetes mellitus; in dogs with clinically relevant hypercalcemia; or in dogs with concurrent malignancy.

LAVERDIA-CA1 can cause hematologic and serum chemistry abnormalities. Dogs should be frequently monitored for evidence of hematologic and serum chemistry abnormalities when initiating and maintaining treatment with LAVERDIA-CA1 (see ADVERSE REACTIONS and TARGET ANIMAL SAFETY).

The safety and effectiveness of LAVERDIA-CA1 has not been evaluated in conjunction with other chemotherapeutic agents or other treatment modalities for lymphoma.

The effect of concomitant medications on the metabolism of LAVERDIA-CA1 has not been evaluated.

The safe use of LAVERDIA-CA1 has not been evaluated in dogs younger than 7 months of age.

The primary metabolism of LAVERDIA-CA1 in vitro and in vivo is thought to be inactivation by glutathione (GSH) conjugation. Therefore, administration of LAVERDIA-CA1 with drugs which undergo substantial GSH conjugation (e.g., acetaminophen) should be minimized.

ADVERSE REACTIONS:

In the field study supporting reasonable expectation of effectiveness, 58 dogs were treated with verdinexor (not commercial formulation) at doses between 1.0 mg/kg and 1.75 mg/kg administered 2 to 3 times a week (see REASONABLE EXPECTATION OF EFFECTIVENESS).

All dogs experienced at least one adverse reaction. The most common adverse reactions across all dose groups included: anorexia, vomiting, diarrhea, weight loss and lethargy. Most adverse reactions were considered Veterinary Cooperative Oncology Group – common terminology criteria for adverse events (VCOG-CTCAE)^1 Grade 1 (mild) or 2 (moderate). Twenty-one dogs experienced a VCOG-CTCAE Grade 3 (severe), 4 (life-threatening), or 5 (death) adverse reaction.

Of the 58 dogs treated with verdinexor, adverse reactions occurring in ≥10% of dogs associated with verdinexor treatment included:

- General: lethargy, fever, weakness, generalized pain
- Gastrointestinal: anorexia, vomiting, diarrhea
- Renal: polyuria, polydipsia, hematuria, proteinuria, low urine specific gravity, urinary tract infection
- Hepatic: elevated liver enzymes, bilirubinuria
- Cardiorespiratory: cough/dyspnea
- Metabolic: weight loss
- Hematologic:thrombocytopenia, anemia, lymphopenia, neutrophilia, leukopenia, eosinopenia, neutropenia, monocytosis, leukocytosis, prolonged partial thromboplastin time, elevated blood urea nitrogen, hypercalcemia, hyperphosphatemia
- Skin: subcutaneous edema/swelling, pyoderma

Adverse reactions occurring in <10% of dogs associated with verdinexor treatment included:

- Renal: protein losing nephropathy, urinary incontinence
- Hepatic: hepatomegaly, elevated bilirubin, icterus
- Cardiorespiratory: heart murmur, arrhythmia,heart block
- Hematologic: hypoglubulinemia, hypoproteinemia, hypoalbuminemia, prolonged prothrombin time
- Neurologic: seizure, tremor, disorientation
- Ocular: corneal opacity
- Skin: bruising, erythema, alopecia
- Other: nasal discharge, epistaxis, lymphadenitis

Thrombocytopenia

Thrombocytopenia (VCOG-CTCAE Grade 1 and 2) was observed in verdinexor treated dogs in the study supporting reasonable expectation of effectiveness. Two dogs with thrombocytopenia during the study were reported with bruising and one dog with thrombocytopenia was reported with epistaxis. In human studies of a closely related compound, idiosyncratic reductions in platelets (severe or medically significant but not immediately life-threatening in 10-20% of patients) were reported.

Protein losing nephropathy

One dog was reported with a protein losing nephropathy (PLN). Two additional dogs, though not reported, may have had a PLN. One dog was reported with hypoalbuminemia and proteinuria on study day 21 which progressed until study end (study day 194). Another dog was reported with proteinuria at study day 7 which persisted (and worsened) to the end of the study (study day 105). At the start of the study the dog had hyperalbuminemia; by study day 105 the dog had hypoalbuminemia.

CONTACT INFORMATION:

To report suspected adverse events, for technical assistance, or to obtain a copy of the Safety Data Sheet (SDS) contact Dechra Veterinary Products at (866) 933-2472.

For additional information about adverse drug experience reporting for animal drugs, contact FDA at 1-888-FDA-VETS or at www.fda.gov/reportanimalae.

INFORMATION FOR DOG OWNERS:

Always provide the Client Information Sheet with each prescription and review it with the dog owner or person responsible for care of the dog. Advise dog owners about possible adverse reactions, when to contact a veterinarian, how to handle and administer the product, and how to clean up any feces, urine, vomit, or saliva from dogs treated with LAVERDIA-CA1 (verdinexor tablets). The Client Information Sheet also contains warnings for humans and what to do in case of accidental human exposure to LAVERDIA-CA1.

CLINICAL PHARMACOLOGY:

Mechanism of action

Verdinexor is a reversible, selective inhibitor of CRM1-mediated nuclear export (SINE) that specifically blocks Chromosome Region Maintenance 1 (CRM1, also known as XPO1). Verdinexor inhibits the export of Tumor Suppressor Proteins (TSP) and Growth Regulatory Proteins (GRP) from the nucleus where they carry out their normal functions; it is selectively cytotoxic for cells with genomic damage (i.e. for tumor cells).

Pharmacokinetics

Verdinexor administered orally is well absorbed in dogs and achieves therapeutic levels (>0.5 to 1.0 μM) with doses of 1 to 3 mg/kg. Following oral administration of a preliminary formulation of verdinexor three times per week for 13 weeks to fed healthy young adult Beagle dogs, overall mean exposure in terms of area under the plasma concentration time curve from time zero to the last quantifiable plasma concentration (AUClast) and maximum plasma concentration (Cmax) showed an increase from 1.25 mg/kg to 1.5 mg/kg; however, exposure at 1.75 mg/kg was either similar or lower than exposure for the 1.5 mg/kg dose group on both evaluation days. The increase in exposure as assessed by dose normalized AUClast and dose normalized Cmax was approximately dose proportional from 1.25 mg/kg to 1.5 mg/kg and less than dose proportional from 1.5 mg/kg to 1.75 mg/kg in males on both evaluation days. In females, the increase in AUClast and Cmax was greater than dose proportional from 1.25 mg/kg to 1.5 mg/kg and there was minimal increase in exposure from 1.5 mg/kg to 1.75 mg/kg on both evaluation days.

Time to maximum plasma concentration (Tmax) was typically reached between 1.1 and 2.5 hours post-dose under fed conditions and there were no differences in Tmax related to sex, dosage, or evaluation day. In general, the terminal elimination half-life for all dose groups was similar, regardless of sex, dosage, or evaluation day and ranged from approximately 2.0 to 4.0 hours.

Inter-animal variability was relatively high in all dose groups (%CV ranging from 16% to 81% for AUClast), so care should be taken in assessing actual pharmacokinetic differences or trends observed.

Following oral administration of a preliminary formulation of verdinexor to fed and fasted dogs, there was a significant food effect on the pharmacokinetics of verdinexor with a 3-fold and 5-fold increase in AUC and Cmax, respectively, when verdinexor was administered orally in the presence of food. Time to reach Cmax (Tmax) was markedly more variable (1-18 hours) when dogs were dosed under fasted conditions as compared to when verdinexor was administered under fed conditions (1.1-2.5 hours).

REASONABLE EXPECTATION OF EFFECTIVENESS:

LAVERDIA-CA1 is conditionally approved pending a full demonstration of effectiveness.

Additional information for Conditional Approvals can be found by searching https://www.fda.gov for "animal conditional approval".

A field study was used to demonstrate a reasonable expectation of effectiveness for LAVERDIA-CA1 for the treatment of lymphoma in dogs.

An open-label, single arm, multicenter field study was conducted to evaluate the effectiveness and safety of verdinexor tablets (not commercial formulation). The study enrolled 58 client-owned dogs with lymphoma either newly diagnosed (n=35), or in first relapse following completion of one chemotherapy regimen (n=23). Treatment groups were designated by the following verdinexor dose regimens: 1.5 mg/kg 3 times weekly; 1.25 mg/kg 3 times weekly; or 1.25 mg/kg 2 times weekly then increased to 1.5 mg/kg twice weekly if well-tolerated. Dose increases and decreases, including changes in dosing amount (mg/kg) and dosing frequency (2 versus 3 times per week) were allowed based on drug tolerability and response to treatment. Response to treatment was evaluated using Veterinary Cooperative Oncology Group (VCOG) response criteria for peripheral lymphoma in dogs (v1.0).^2

For all dogs enrolled, median time to progression (TTP) was 29.5 days (range 7-244 days). The median TTP for the naïve and first relapse cases was 36.5 days (range 7-244 days) and 22 days (range 7-194 days), respectively. The objective response rate (best response of partial or complete response) for all dogs was 34.5% (20/58), distributed proportionately between the naïve (12/35, 34.3%) and first relapse (8/23, 34.8%) subgroups. Among dogs with objective response, the median duration of response was 18 days (range 7-187 days). No clinically significant differences in treatment benefit were noted when comparing dose groups. A subset (n=17, 29%) of the overall enrolled population had a TTP of at least 56 days. Of these 17 dogs, 11 were naïve to treatment and 6 had relapsed lymphoma; 5 had T-cell lymphoma and 12 had B-cell lymphoma. Three dogs, 2 dogs with T-cell lymphoma (1 naïve and 1 relapsed) and 1 dog with B-cell lymphoma naïve to treatment had TTP of 182 days or longer.

During the study, verdinexor was administered concomitantly with other medications such as corticosteroids (prednisone, 39 dogs), proton pump inhibitors, antibiotics, H2 blockers, anti-emetics, gastrointestinal motility modifiers, and opioids.

TARGET ANIMAL SAFETY:

In a 13-week margin of safety study, 32 healthy Beagle dogs (4/sex/group), approximately 7 months old at study initiation, were administered LAVERDIA-CA1 at either 0, 1.0, 1.5, or 1.75 mg/kg of body weight 3 times a week (Monday, Wednesday, and Friday). Dogs in the control group were sham-dosed. Dogs were fed prior to dosing. All dogs survived to study termination.

Dose-dependent LAVERDIA-CA1-related clinical findings included vomiting, inappetence, decreased body condition, decreased body weight, loss of skin elasticity, lacrimation, slight depression, and slight decrease of forelimb strength. Non-dose-dependent LAVERDIA-CA1-related findings included abnormal feces (soft, watery, or mucoid feces), excessive shedding, and sparse hair.

Dogs in the 1.0 mg/kg group and dogs in the 1.5 and 1.75 mg/kg groups had lower body weight values, starting on study days 28 and 21 respectively, that continued to the end of the study compared to control dogs.

Dose-dependent LAVERDIA-CA1-related clinical pathology findings included decreases in chloride and increases in fibrinogen. Non-dose-dependent LAVERDIA-CA1-related clinical pathology findings included decreases in lymphocytes, eosinophils, and monocytes, and increases in albumin and blood urea nitrogen.

Dose-dependent organ weight findings in the LAVERDIA-CA1 treated dogs included lower testes, thymus, and thyroid/parathyroid gland weights. Dose-dependent histopathological findings in the LAVERDIA-CA1 treated dogs included lesions in the testes and epididymides (moderate to marked seminiferous tubules degeneration/atrophy, minimal to moderate vacuolation, and minimal Leydig cell hypertrophy in the testes; and severe oligospermia/germ cell debris in the epididymides) and in the thymus (minimal to mild cortical lymphoid depletion).

HOW SUPPLIED:

LAVERDIA-CA1 is presented as immediate release coated tablets in three dosage strengths, 2.5 mg, 10 mg and 50 mg. The 2.5 mg tablets are supplied in 10-count and 50-count, the 10 mg tablets are supplied in 10-count and 50-count, and the 50 mg tablets are supplied in 16-count and 50-count in an HDPE bottle with a heat sealed, child-resistant cap and a desiccant included in each bottle. The bottles are individually packaged into cartons.

DISPOSAL:

Dispose of any unused product or waste materials in accordance with proper procedures for cytotoxic drugs.

STORAGE INFORMATION:

Store the bottles at controlled room temperature 20° to 25°C (68° – 77°F).

REFERENCES:

1. Veterinary co-operative oncology group – common terminology criteria for adverse events (VCOG-CTCAE) following chemotherapy or biological antineoplastic therapy in dogs and cats v1.1. Vet Compar Onco. 2016, Vol.14(4), p.417-446.

2. Response evaluation criteria for peripheral nodal lymphoma in dogs (v1.0)–a veterinary cooperative oncology group (VCOG) consensus document. Vet Compar Onco. 2010, Vol.8(1), p.28-37.

LAVERDIA is a trademark of Dechra Limited. Dechra is a registered trademark of Dechra Limited.

Manufactured by:
Halo Pharmaceutical, Inc.
(d/b/a Cambrex Whippany)
Whippany, NJ USA

Distributed by:
Dechra Veterinary Products
7015 College Boulevard, Suite 525
Overland Park, KS 66211
(866) 933-2472

Product inquiries should be directed to
Dechra Veterinary Products, (866) 933-2472

Conditionally approved by FDA pending a full
demonstration of effectiveness under application
number 141-526

Issued: February 2022

1894-02
PIN-7001-05

PRINCIPAL DISPLAY PANEL - 2.5 mg Tablet Bottle Carton

LAVERDIA™-CA1
(verdinexor tablets)

2.5 mg per tablet

Antineoplastic
For Oral Use in Dogs Only
Indicated for the treatment of lymphoma in dogs

Conditionally approved by FDA pending a
full demonstration of effectiveness under
application number 141-526

CAUTION: Federal (USA) law restricts this
drug to use by or on the order of a licensed
veterinarian. Use only as directed. It is a
violation of Federal law to use this product
other than as directed in the labeling.

50 Tablets

Dechra

PRINCIPAL DISPLAY PANEL - 10 mg Tablet Bottle Carton

LAVERDIA™-CA1
(verdinexor tablets)

10 mg per tablet

Antineoplastic
For Oral Use in Dogs Only
Indicated for the treatment of lymphoma in dogs

Conditionally approved by FDA pending a
full demonstration of effectiveness under
application number 141-526

CAUTION: Federal (USA) law restricts this
drug to use by or on the order of a licensed
veterinarian. Use only as directed. It is a
violation of Federal law to use this product
other than as directed in the labeling.

50 Tablets

Dechra

PRINCIPAL DISPLAY PANEL - 50 mg Tablet Bottle Carton

LAVERDIA™-CA1
(verdinexor tablets)

50 mg per tablet

Antineoplastic
For Oral Use in Dogs Only
Indicated for the treatment of lymphoma in dogs

Conditionally approved by FDA pending a
full demonstration of effectiveness under
application number 141-526

CAUTION: Federal (USA) law restricts this
drug to use by or on the order of a licensed
veterinarian. Use only as directed. It is a
violation of Federal law to use this product
other than as directed in the labeling.

50 Tablets

Dechra